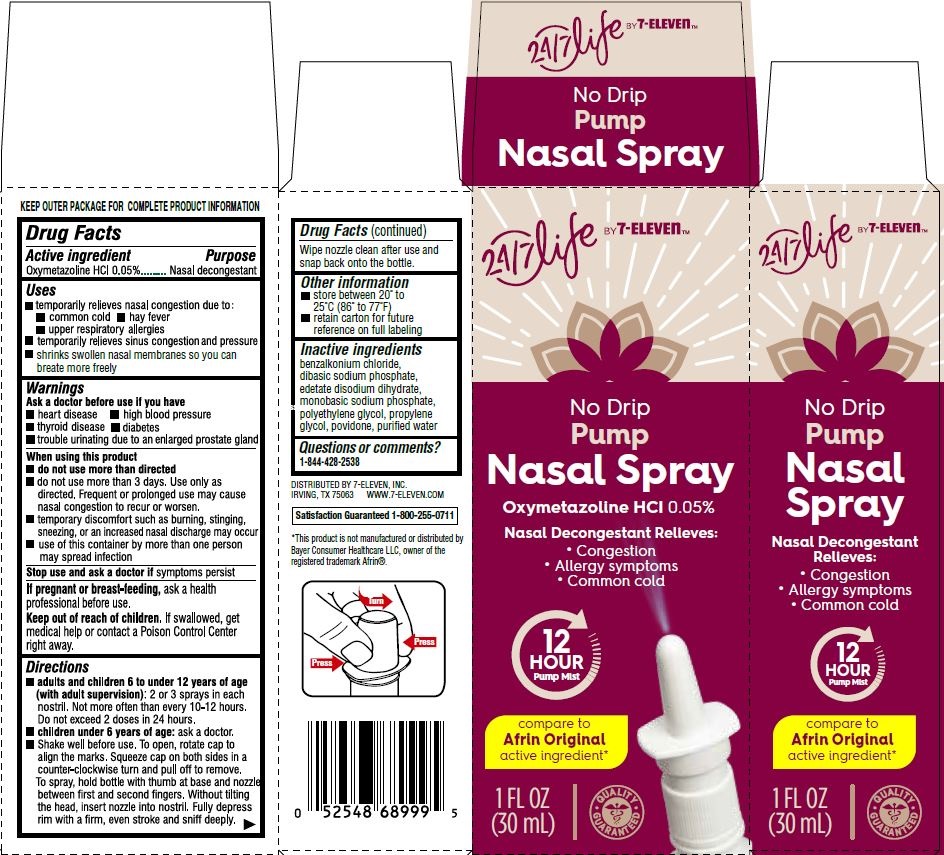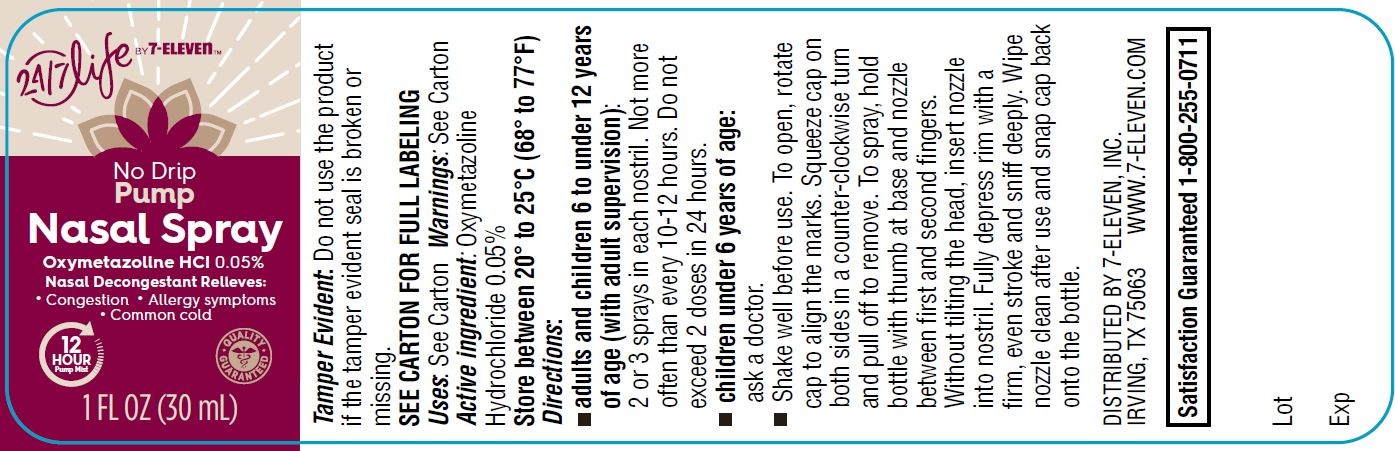 DRUG LABEL: Nasal Spray, 24-7 for Life
NDC: 66715-5626 | Form: SPRAY
Manufacturer: Lil' Drug Store Products, Inc.
Category: otc | Type: HUMAN OTC DRUG LABEL
Date: 20240220

ACTIVE INGREDIENTS: OXYMETAZOLINE HYDROCHLORIDE 0.05 g/100 mL
INACTIVE INGREDIENTS: WATER; EDETATE DISODIUM; PROPYLENE GLYCOL; POVIDONE, UNSPECIFIED; SODIUM PHOSPHATE, MONOBASIC, UNSPECIFIED FORM; POLYETHYLENE GLYCOL, UNSPECIFIED; SODIUM PHOSPHATE, DIBASIC, UNSPECIFIED FORM; BENZALKONIUM CHLORIDE

Nasal Spray, Pump, 24/7 for Life by 7-ELEVENTM

Drug Facts

Active ingredient

Oxymetazoline HCl 0.05%

Purpose

Nasal decongestant

Uses

- temporarily relieves nasal congestion due to:
- common cold
- hay fever
- upper respiratory allergies
- temporarily relieves sinus congestion and pressure
- shrinks swollen nasal membranes so you can breathe more freely

Warnings

Ask a doctor before use if you have

- heart disease
- high blood pressure
- thyroid disease
- diabetes
- trouble urinating due to an enlarged prostate gland

When using this product

- do not use more than directed
- do not use for more than 3 days. Use only as directed. Frequent or prolonged use may cause nasal congestion to recur or worsen.
- temporary discomfort such as burning, stinging, sneezing or an increase in nasal discharge may occur.
- use of this container by more than one person may spread infection.

Stop use

Stop use and ask a doctor if symptoms persist.

If pregnant or breast-feeding, ask a health professional before use.

Keep out of reach of children. If swallowed, get medical help or contact a Poison Control Center right away.

Directions

- adults and children 6 to under 12 years of age (with adult supervision): 2 or 3 sprays in each nostril not more often than every 10 to 12 hours. Do not exceed 2 doses in any 24-hour period.
- children under 6 years of age: consult a doctor
- Shake well before use. To open, rotate cap to align the marks. Squeeze cap on both sides in a counter-clockwise turn and pull off to remove. To spray, hold bottle between thumb at base and nozzle between first and second fingers. without tilting the head, insert nozzle into nostril. Fully depress rim with a firm, even stroke and sniff deeply. Wipe nozzle clean after use and snap cap back onto the bottle.

Other information

- store between 20-25°C (68-77°F)
- retain carton for future reference on full labeling

Inactive ingredients

benzalkonium chloride, dibasic sodium phosphate, edetate disodium dihydrate, monobasic sodium phosphate, polyethylene glycol, propylene glycol, povidone, purified water

Questions or comments?

call toll free 1-877-507-6516

(M-F 8AM-4:30PM CST)

DISTRIBUTED BY 7-ELEVEN, INC.
IRVING, TX 75063 WWW.7-ELEVEN.COM

Satisfaction Guaranteed 1-800-255-0711

*This product is not manufactured or distributed by
Bayer Consumer Healthcare LLC, owner of the
registered trademark Afrin®.

Nasal Spray , Pump, 24/7 for Life by 7-ELEVENTM - PDP/Package

[7-ELEVEN logo]

No Drip

Pupm

Nasal Spray

Oxymetazoline HCl 0.05%

Nasal Decongestant Relieves:

- Congestion
- Allergy Symptoms
- Common Cold

12

HOUR

Pump Mist

compare to

Afrin Original

active ingredient*

1 FL OZ

(30 mL)

[caduceus]

[spray nozzle image]